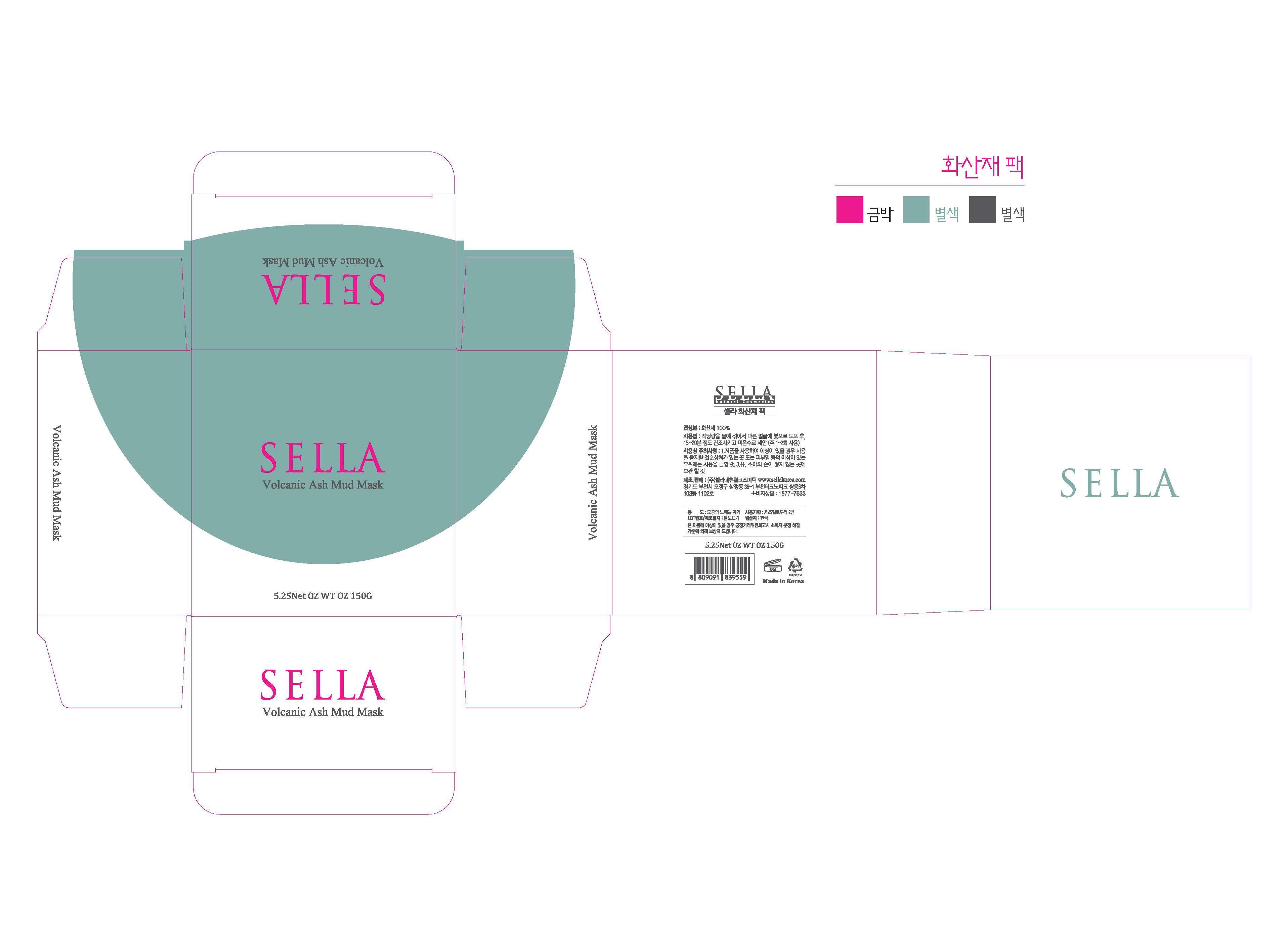 DRUG LABEL: SELLA NATURAL VOLCANIC ASH  MUD MASK
NDC: 69603-1301 | Form: POWDER
Manufacturer: Sella Natural Cosmetics Co.,Ltd.
Category: otc | Type: HUMAN OTC DRUG LABEL
Date: 20150111

ACTIVE INGREDIENTS: SILANOL 34.1 g/100 g
INACTIVE INGREDIENTS: ALUMINUM OXIDE; SODIUM OXIDE

Drug Facts

ACTIVE INGREDIENT

SiO2

INACTIVE INGREDIENT

Al2O3, Na2O, Fe2O3, CaO, M2O, TiO2, ZrO2 etc

PURPOSE

skin protectant
anti oxidant

keep out of reach of the children

INDICATIONS AND USAGE

1. place on spoon ful of the volcanic ash powder in the mixing container
2. add purified water until it the water level reaches the line
3. get the lid on the mixing container and shake to mix well
4. wash face with sella cheansing bar three times
5. dry for 20 to 25 minutes, then wash off with warm water
6. apply sell gold serum and essence cream

WARNINGS

・Stop using the product when you have skin problems or the product disagrees with your skin
・Stop using the product immediately and consult a dermatologist if you have redness, swelling, itching or irritation on the skin while or after using the product.
・Don't place the product in any place where it will be subjected to extremely high or low temperatures or direct sunlight.

DOSAGE AND ADMINISTRATION

for external use only